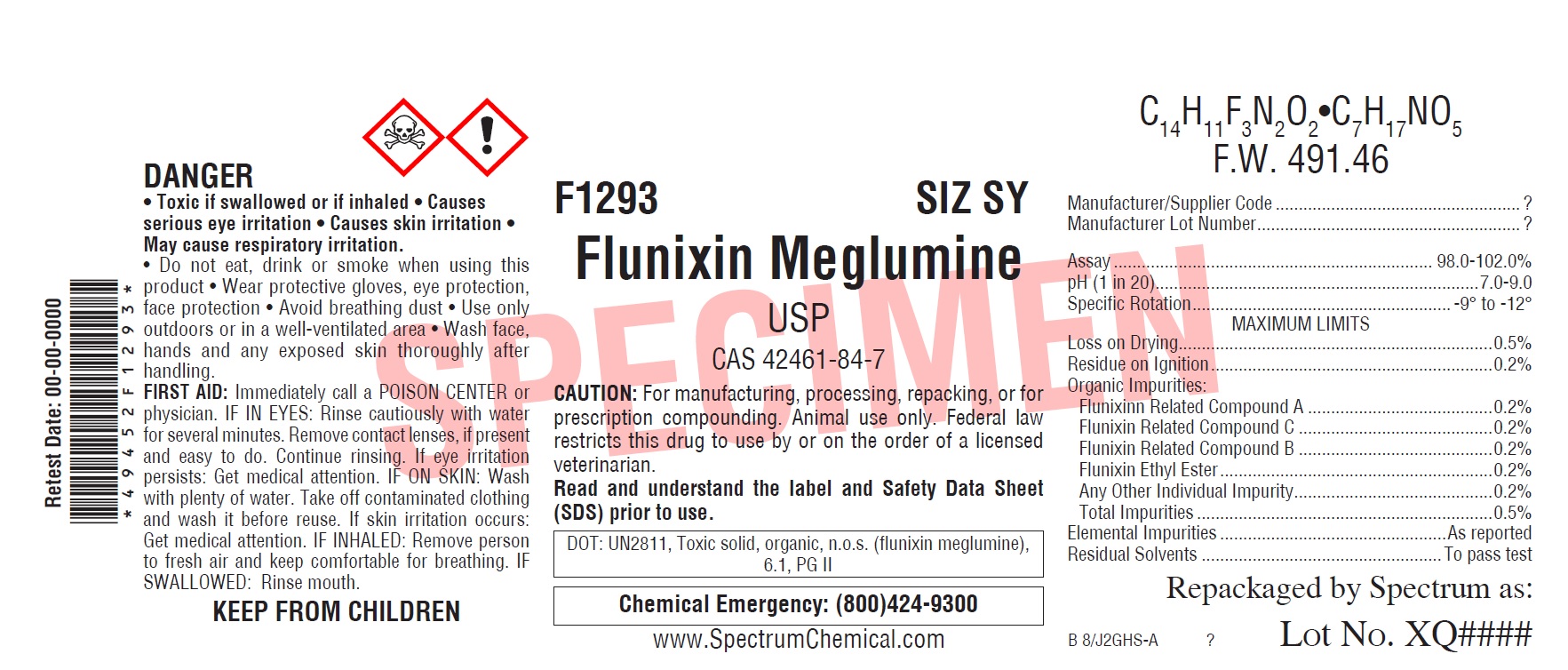 DRUG LABEL: Flunixin Meglumine
NDC: 49452-3153 | Form: POWDER
Manufacturer: Spectrum Laboratory Products, Inc.
Category: other | Type: BULK INGREDIENT
Date: 20210126

ACTIVE INGREDIENTS: FLUNIXIN MEGLUMINE 1 g/1 g

Flunixin Meglumine